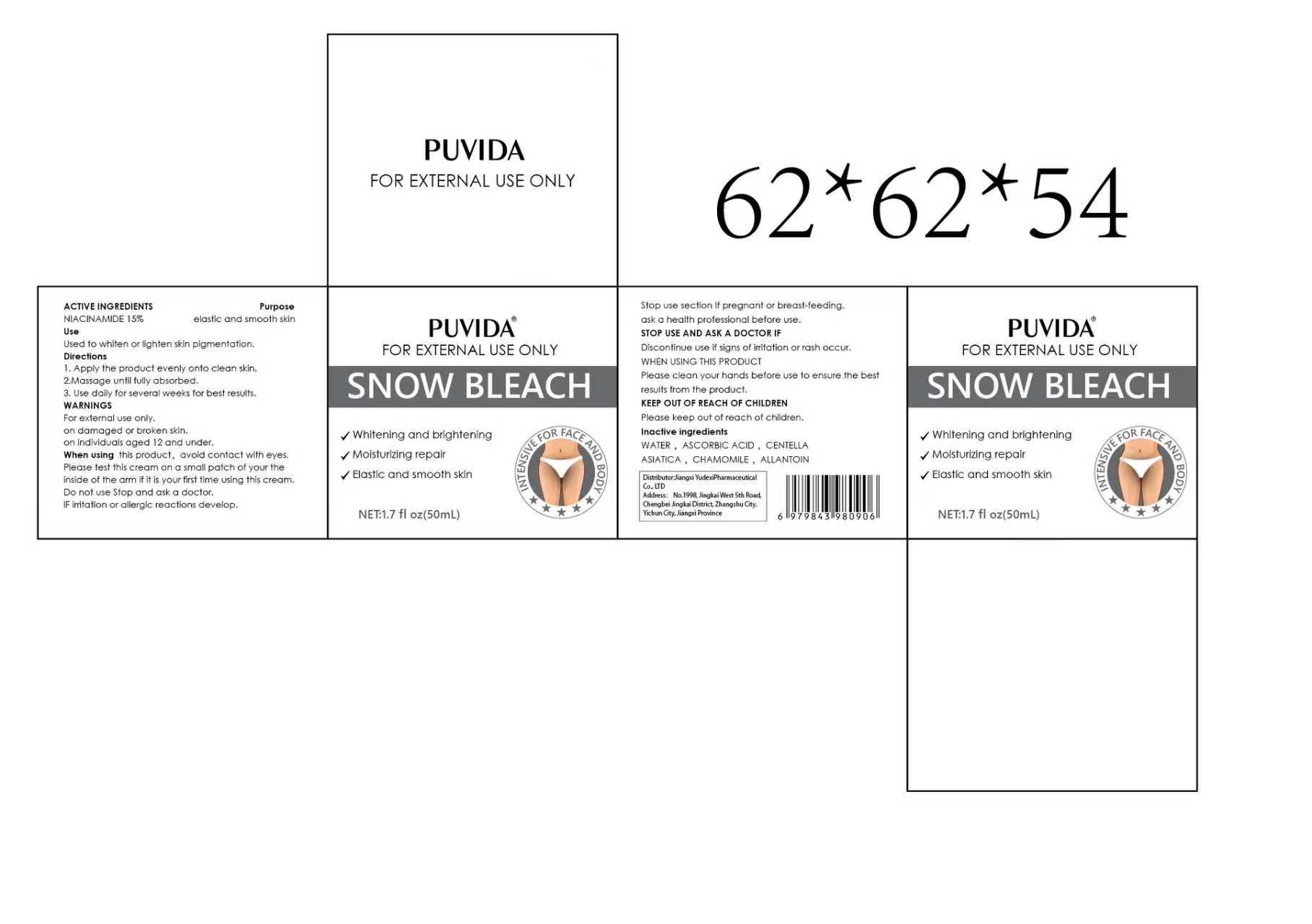 DRUG LABEL: PUVIDA SNOW BLEACH
NDC: 85248-093 | Form: CREAM
Manufacturer: Jiangxi Yudexi Pharmaceutical Co., LTD
Category: otc | Type: HUMAN OTC DRUG LABEL
Date: 20260207

ACTIVE INGREDIENTS: NIACINAMIDE 15 g/100 mL
INACTIVE INGREDIENTS: ASCORBIC ACID; CENTELLA ASIATICA WHOLE; CHAMOMILE; WATER; ALLANTOIN

85248-093

Active Ingredient

NIACINAMIDE 15%

Purpose

elastic and smooth skin

Use

Used to whiten or lighten skin pigmentation.

Warnings

For external use only. on damaged or broken skin. on individwals aged 12 and under.

Do not use Stop and ask a doctor. IF irritation or allergic reactions develop.

When Using

When using this product, avoid contact with eyes confact with eyes. Please test this cream on a small patch of your the inside of the arm if it is your first time using this cream.

Stop Use

Stop use section lf pregnant or breast-feeding. ask a health professional before use.

Ask Doctor

Discontinue use if signs of irritation or rash occur.WHEN USING THIS PRODUCT Please clean your hands before use to ensure the best results from the product.

Keep Oot Of Reach Of Children

Please keep out of reach of children.

Directions

1.Apply the product evenly onto clean skin. 2.Massage until fully absorbed. 3. Use daily for several weeks for best results.

Inactive ingredients

WATER , ASCORBIC ACID ，CENTELLA ASIATICA ，CHAMOMILE ，ALLANTOIN